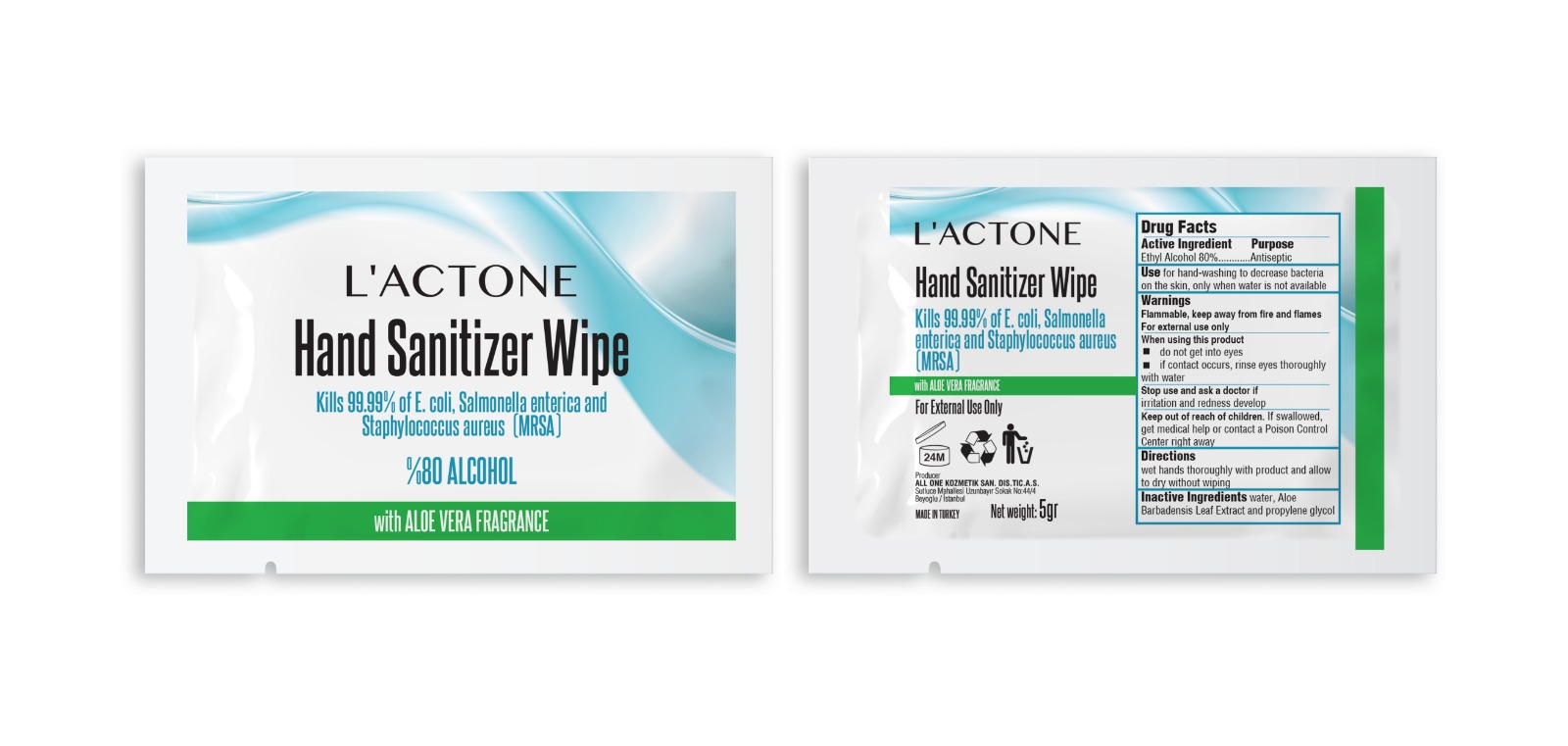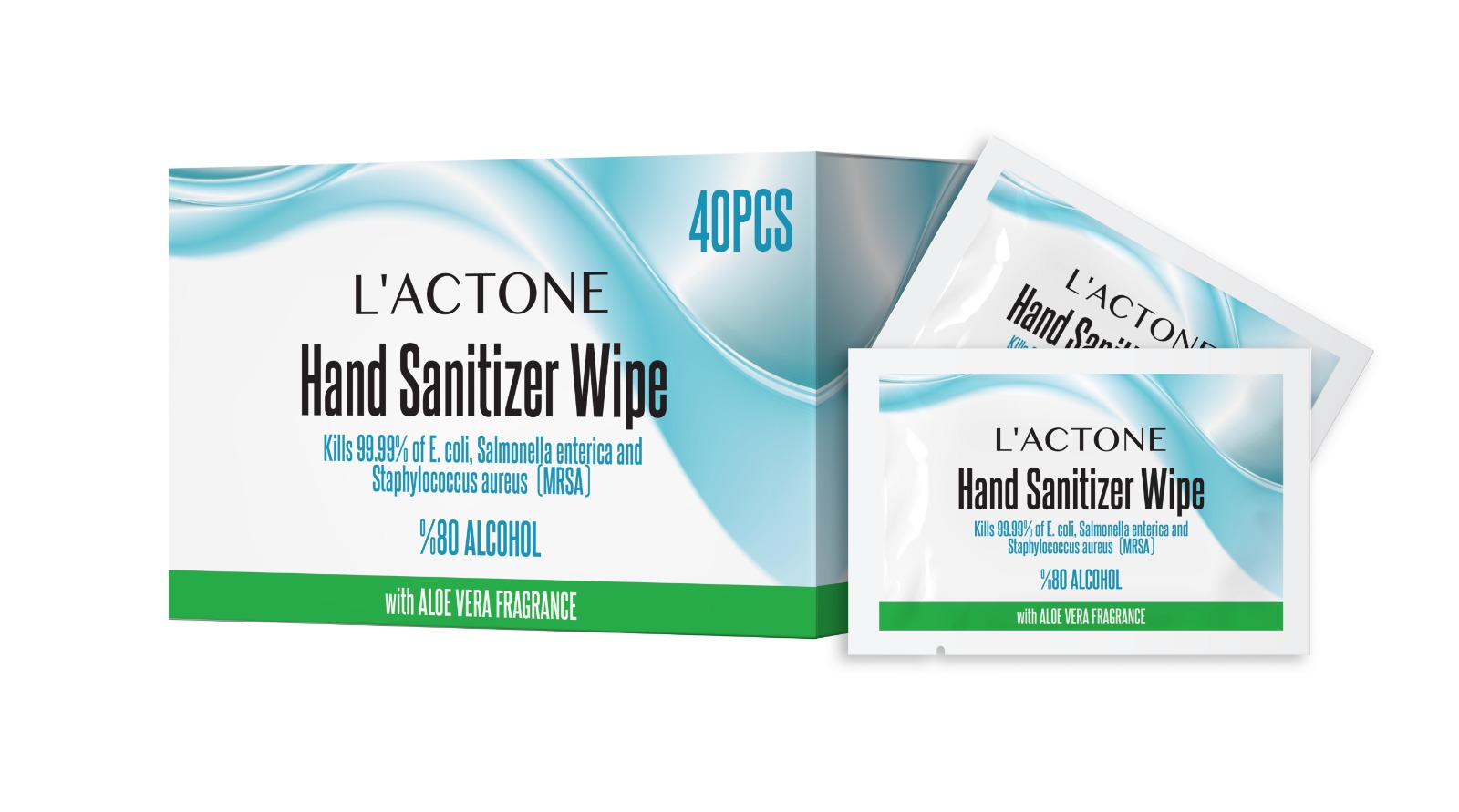 DRUG LABEL: LACTONE HAND SANITIZER WIPE
NDC: 75348-888 | Form: CLOTH
Manufacturer: ALL ONE KOZMETIK SANAYI DIS TICARET ANONIM SIRKETI
Category: otc | Type: HUMAN OTC DRUG LABEL
Date: 20200618

ACTIVE INGREDIENTS: ALCOHOL 800 mg/1 g
INACTIVE INGREDIENTS: ALOE VERA LEAF; PROPYLENE GLYCOL; WATER

Hand Sanitizer Wipes

Active Ingredient(s)

Ethyl Alcohol 80%

Purpose

Antiseptic

Use

Use for hand-washing to decrease bacteria on the skin, only when water is not available

Warnings

Flammable, keep away from heat and flames. For external use only

When using this product

do not get into eyes

if contact occurs, rinse eyes thoroughly with water

Stop use and ask a doctor if irritation or rash occurs.

Keep out of reach of children. If swallowed, get medical help or contact a Poison Control Center right away.

Directions

wet hands thorougly with product and allow to dry without wiping

Inactive ingredients

water, Aloe Barbadensis Leaf Extract and propylene glycol

Package Label - Principal Display Panel

Producer

ALL ONE KOZMETIK SAN. VE DIS. TIC. A. S.

Sutluce Mahallesi

Uzunbayır Sokak No:44/4

Beyoglu/Istanbul

Net weight: 5 gr

MADE IN TURKEY

Hand Sanitizer Wipe

Kills 99.99% of E. coli, Salmonella enterica and Staphylococcus aureus (MRSA)

with ALOE VERA FRAGRANCE

For External Use only

LACTONE HAND SANITIZING WIPES- alcohol cloth